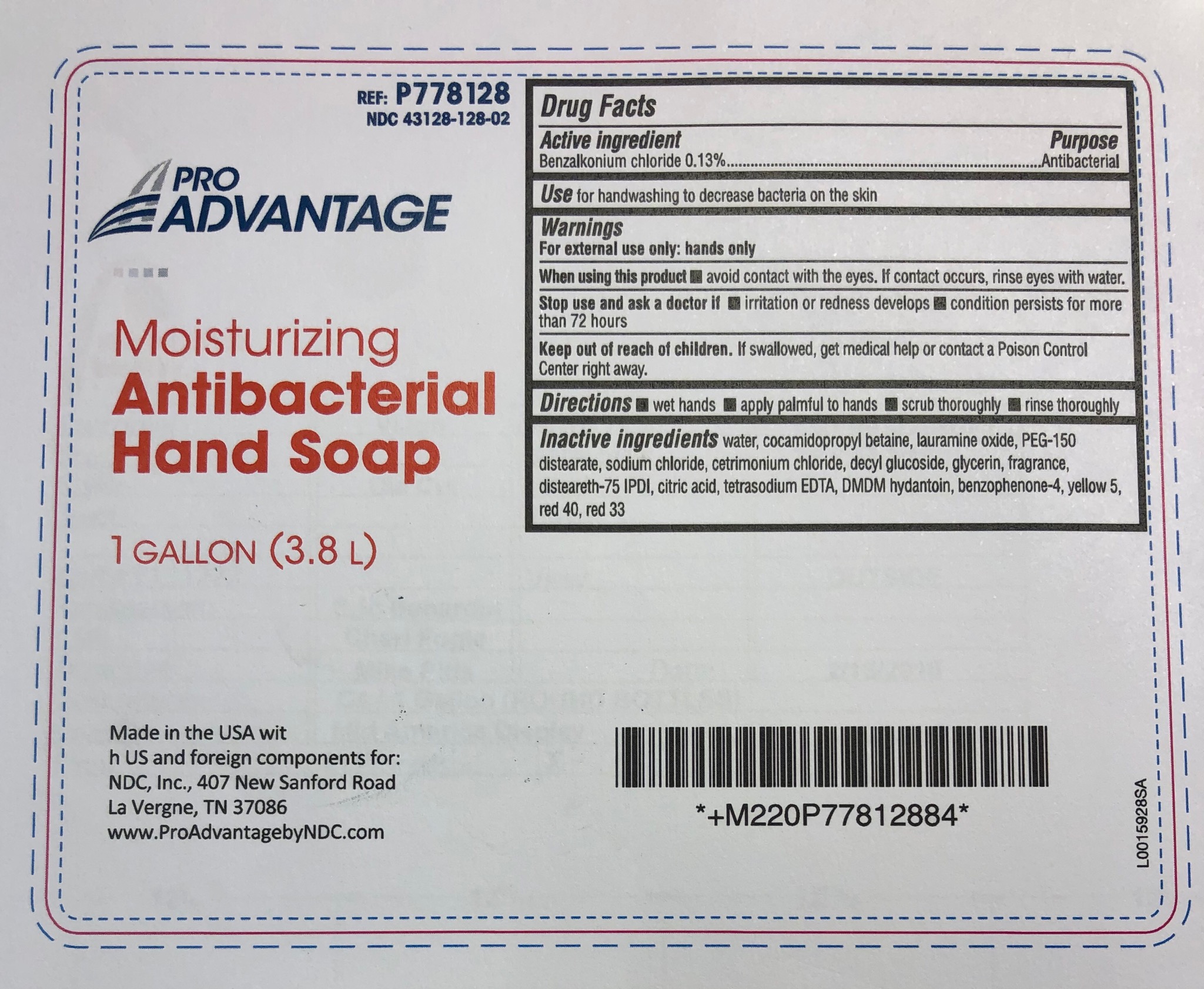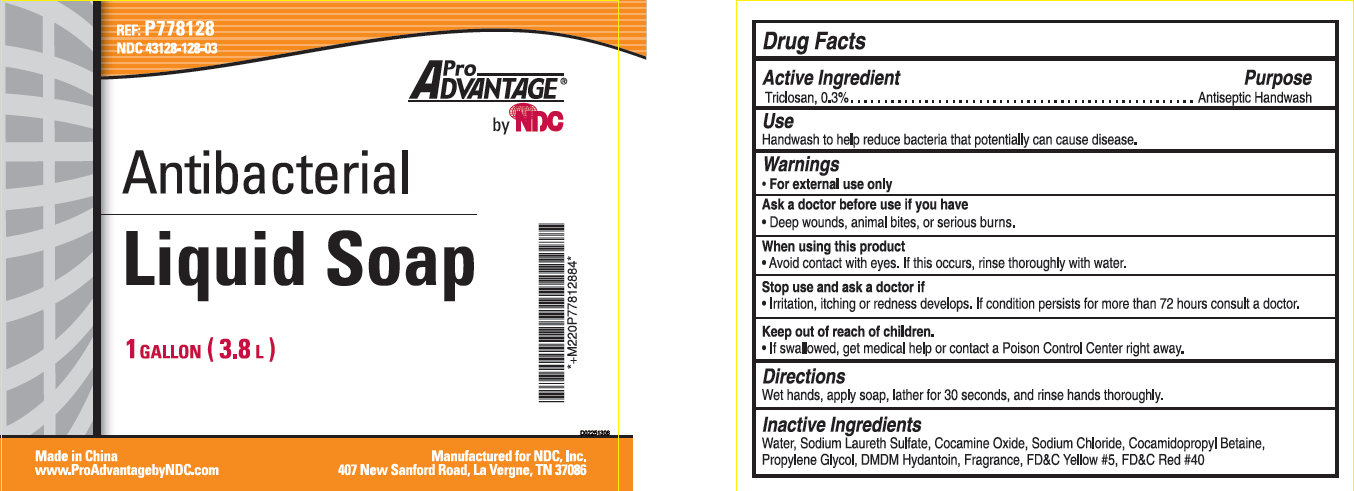 DRUG LABEL: Pro Advantage Antibacterial
NDC: 43128-128 | Form: LIQUID
Manufacturer: NDC National Distribution & Contracting, Inc.
Category: otc | Type: HUMAN OTC DRUG LABEL
Date: 20230315

ACTIVE INGREDIENTS: TRICLOSAN 3 mg/0.001 L
INACTIVE INGREDIENTS: WATER; SODIUM LAURETH-3 SULFATE; COCAMINE OXIDE; SODIUM CHLORIDE; COCAMIDOPROPYL BETAINE; PROPYLENE GLYCOL; DMDM HYDANTOIN; FD&C YELLOW NO. 5; FD&C RED NO. 40

Pro Advantage Antibacterial Liquid Soap

Active Ingredient

Triclosan, 0.3%

Purpose

Antiseptic Handwash

Use

Handwash to help reduce bacteria that potentially can cause disease.

Warnings

• For external use only

Ask a doctor before use if you have

• Deep wounds, animals bites, or serious burns.

When using this product

• Avoid contact with eyes. If this occurs, rinse thoroughly with water.

Stop use and ask a doctor if

• Irritation, itching or redness develops. If condition persists for more than 72 hours consult a doctor.

Keep out of reach of children.

• If swallowed, get medical help or contact a Poison Control Center right away.

Directions

Wet hands, apply soap, lather for 30 seconds, and rinse hands thoroughly.

Inactive Ingredients

Water, Sodium Laureth Sulfate, Cocamine Oxide, Sodium Chloride, Cocamidopropyl Betaine, Propylene Glycol, DMDM Hydantoin, Fragrance, FDandC Yellow 5, FDandC Red 40

REF: P778128 NDC 43128-108-03

Made in China
www.ProAdvantagebyNDC.com
Manufactured for NDC, Inc.
407 New Sanford Road, La Vergne, TN 37086